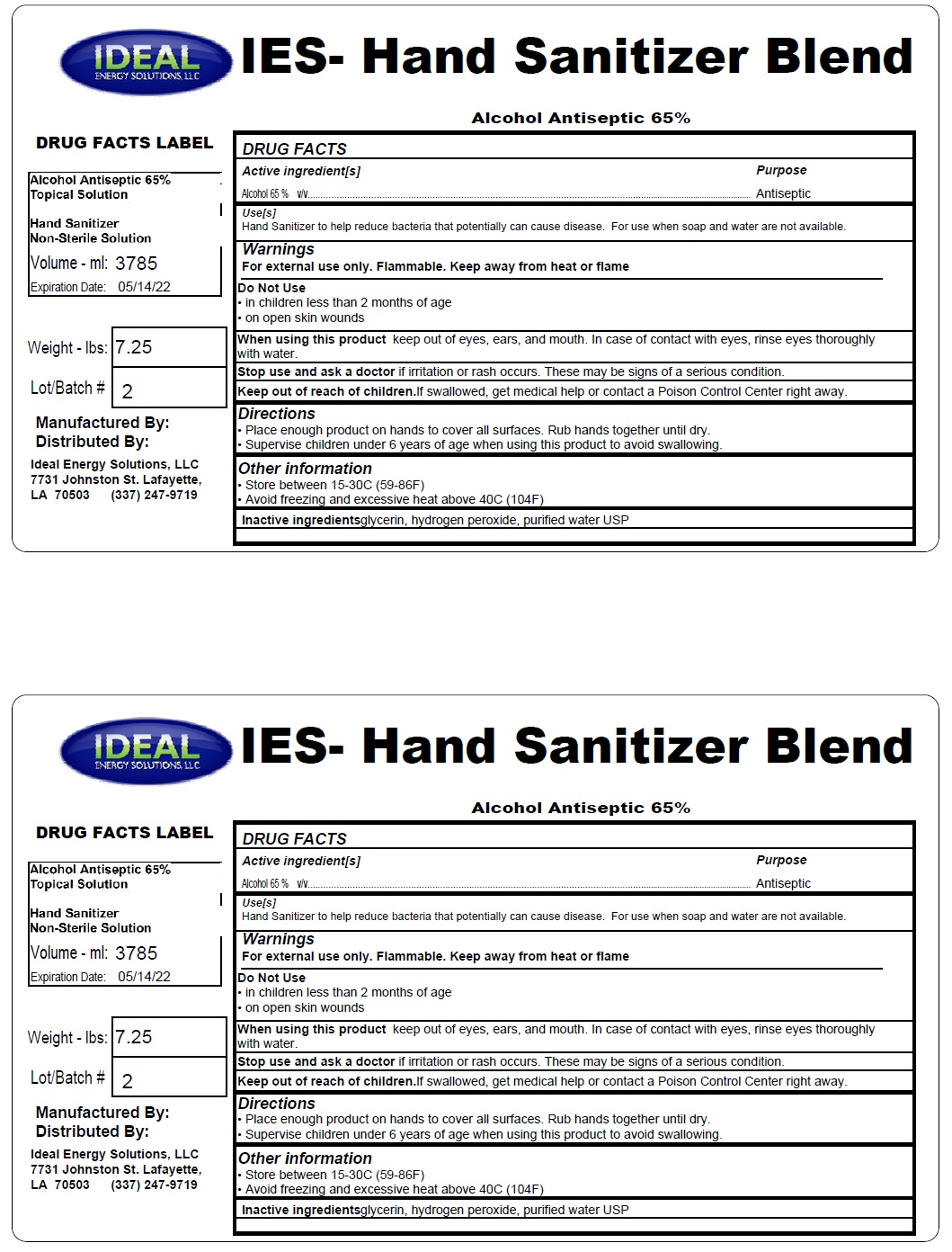 DRUG LABEL: IES- Hand Sanitizer Blend
NDC: 77910-001 | Form: LIQUID
Manufacturer: Ideal Energy Solutions LLC
Category: otc | Type: HUMAN OTC DRUG LABEL
Date: 20200514

ACTIVE INGREDIENTS: ALCOHOL 65 mL/100 mL; ISOPROPYL ALCOHOL 4 mg/100 mL
INACTIVE INGREDIENTS: WATER; GLYCERIN; POLYSORBATE 80; CARBOMER HOMOPOLYMER TYPE C (ALLYL PENTAERYTHRITOL CROSSLINKED); LEMON OIL

IES- Hand Sanitizer Blend

Active ingredient

Alcohol 65% v/v

Purpose

Antiseptic

Warnings

For external use only. Flammable. Keep away from heat or flame

Do Not Use

• in children less than 2 months of age
• on open skin wounds

When using this product keep out of eyes, ears, and mouth. In case of contact with eyes, rinse eyes thoroughly
with water.

Stop use and ask a doctor if irritation or rash occurs. These may be signs of a serious condition.

Keep out of reach of children.If swallowed, get medical help or contact a Poison Control Center right away.

uses

Hand Sanitizer to help reduce bacteria that potentially can cause disease. For use when soap and water are not available.

Directions

• Place enough product on hands to cover all surfaces. Rub hands together until dry.
• Supervise children under 6 years of age when using this product to avoid swallowing.

Other information

• Store between 15-30C (59-86F)
• Avoid freezing and excessive heat above 40C (104F)

Inactive Ingredient

glycerin, hydrogen peroxide, purified water USP